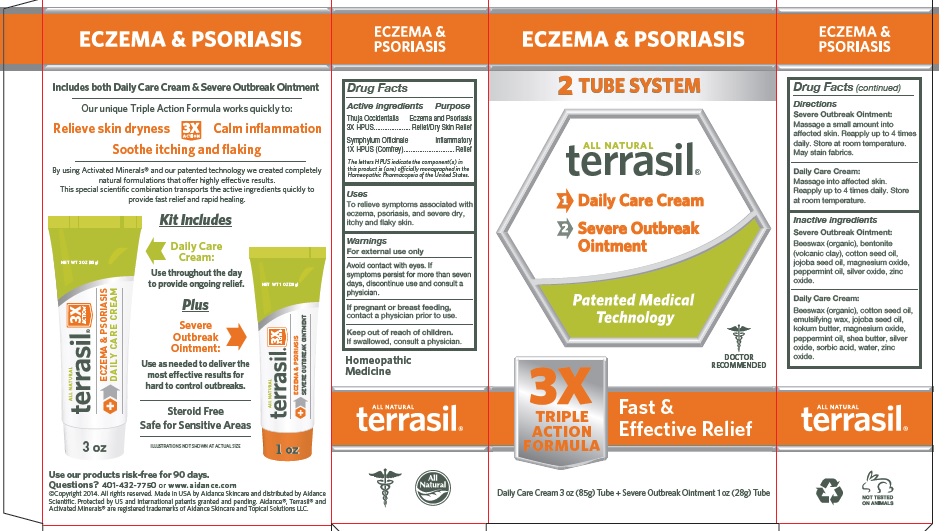 DRUG LABEL: Terrasil Eczema and Psoriasis
NDC: 24909-167 | Form: KIT | Route: TOPICAL
Manufacturer: Aidance Skincare & Topical Solutions, LLC
Category: homeopathic | Type: HUMAN OTC DRUG LABEL
Date: 20240524

ACTIVE INGREDIENTS: THUJA OCCIDENTALIS LEAFY TWIG 3 [hp_X]/1 g; SYMPHYTUM OFFICINALE WHOLE 1 [hp_X]/1 g; THUJA OCCIDENTALIS LEAFY TWIG 3 [hp_X]/1 g; SYMPHYTUM OFFICINALE WHOLE 1 [hp_X]/1 g
INACTIVE INGREDIENTS: WHITE WAX; COTTONSEED OIL; CETOSTEARYL ALCOHOL; POLYSORBATE 60; JOJOBA OIL; GARCINIA INDICA SEED BUTTER; MAGNESIUM OXIDE; PEPPERMINT OIL; SHEA BUTTER; SILVER OXIDE; SORBIC ACID; ZINC OXIDE; BENTONITE; COTTONSEED OIL; JOJOBA OIL; MAGNESIUM OXIDE; PEPPERMINT OIL; SILVER OXIDE; WHITE WAX; ZINC OXIDE

24909-167 terrasil Eczema and Psoriasis

Active Ingredient

Thuja Occidentalis 3X HPUS, Symphytum Officinale (Comfrey) 1X HPUS
The letters HPUS indicate the component(s) in this product is (are) officially monographed in the Homeopathic Pharmacopeia of the United States

Purpose

Thuja Occidentalis - Eczema & Psoriasis Relief / Dry Skin Relief
Symphytum Officinale (Comfrey) - Inflammatory Relief

Uses

To relieve symptoms associated with eczema, psoriasis, and severe dry, itchy and flaky skin.

Warnings

For external use only

Avoid contact with eyes. If symptoms persist for more than seven days, discontinue use and consult a physician.

If pregnant or breast feeding, contact a physician prior to use.

Keep out of reach of children.

If swallowed, consult a physician.

Directions

Severe Outbreak Ointment:Massage a small amount into affected skin. Reapply up to 4 times daily.
Store at room temperature. May stain fabrics.
Daily Care Cream:Massage into affected skin. Reapply up to 4 times daily. Store at room temperature.

Inactive Ingredients

Severe Outbreak Ointment:Beeswax (organic), bentonite (volcanic clay), cotton seed oil, jojoba seed oil, magnesium oxide, peppermint oil, silver oxide, zinc oxide.

Daily Care Cream:Beeswax (organic), cotton seed oil, emulsifying wax, jojoba seed oil, kokum butter, magnesium oxide, peppermint oil, shea butter, silver oxide, sorbic acid, water, zinc oxide.

PRINCIPAL DISPLAY PANEL - BOX

ECZEMA & PSORIASIS
2 Tube System

All Natural

terrasil

1 > Daily Care Cream

2 > Severe Outbreak Ointment

Patented Medical Technology

3X TRIPLE ACTION FORMULA - Fast & Effective Relief